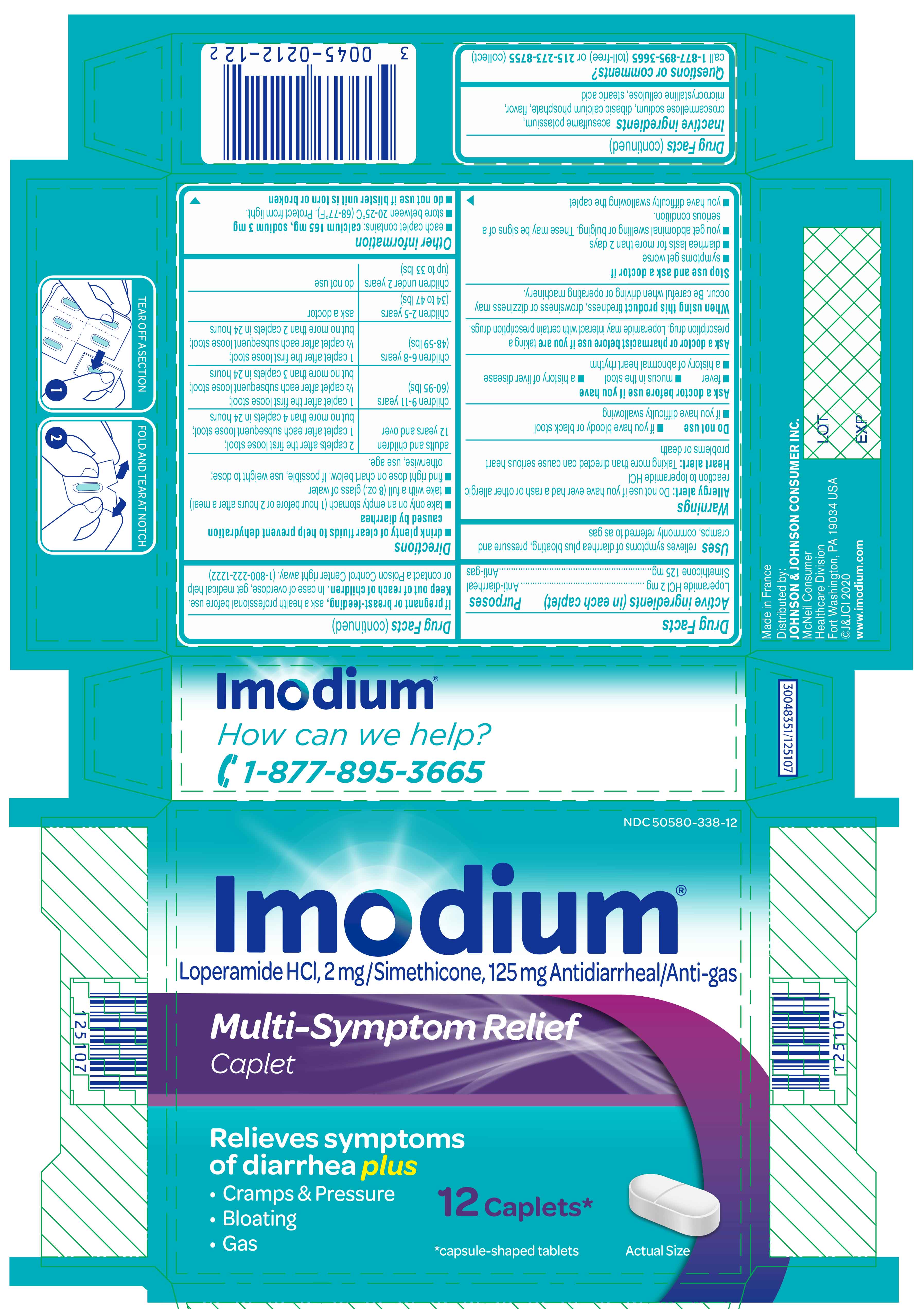 DRUG LABEL: IMODIUM
NDC: 50580-338 | Form: TABLET
Manufacturer: Kenvue Brands LLC
Category: otc | Type: HUMAN OTC DRUG LABEL
Date: 20260123

ACTIVE INGREDIENTS: LOPERAMIDE HYDROCHLORIDE 2 mg/1 1; DIMETHICONE 125 mg/1 1
INACTIVE INGREDIENTS: CROSCARMELLOSE SODIUM; ACESULFAME POTASSIUM; ANHYDROUS DIBASIC CALCIUM PHOSPHATE; MICROCRYSTALLINE CELLULOSE; STEARIC ACID

IMODIUM
Multi-Symptom Relief

Drug Facts

ACTIVE INGREDIENT

PURPOSE

Active ingredients (in each caplet) | Purposes
Loperamide HCl 2 mg | Anti-diarrheal
Simethicone 125 mg | Anti-gas

Uses

relieves symptoms of diarrhea plus bloating, pressure and cramps, commonly referred to as gas

Warnings

Allergy alert

Do not use if you have ever had a rash or other allergic reaction to loperamide HCl

Heart alert

Taking more than directed can cause serious heart problems or death

Do not use

- if you have bloody or black stool
- if you have difficulty swallowing

Ask a doctor before use if you have

- fever
- mucus in the stool
- a history of liver disease
- a history of abnormal heart rhythm

Ask a doctor or pharmacist before use if you are taking a prescription drug. Loperamide may interact with certain prescription drugs.

When using this product tiredness, drowsiness or dizziness may occur. Be careful when driving or operating machinery.

Stop use and ask a doctor if

- symptoms get worse
- diarrhea lasts for more than 2 days
- you get abdominal swelling or bulging. These may be signs of a serious condition.
- you have difficulty swallowing the caplet

PREGNANCY OR BREAST FEEDING

If pregnant or breast-feeding, ask a health professional before use.

Keep out of reach of children. In case of overdose, get medical help or contact a Poison Control Center right away. (1-800-222-1222)

Directions

- drink plenty of clear fluids to help prevent dehydration caused by diarrhea
- take only on an empty stomach (1 hour before or 2 hours after a meal)
- take with a full (8 oz.) glass of water
- find right dose on chart below. If possible, use weight to dose; otherwise, use age.
  adults and children 12 years and over | 2 caplets after the first loose stool; 1 caplet after each subsequent loose stool; but no more than 4 caplets in 24 hours
  children 9-11 years (60-95 lbs) | 1 caplet after the first loose stool; ½ caplet after each subsequent loose stool; but no more than 3 caplets in 24 hours
  children 6-8 years (48-59 lbs) | 1 caplet after the first loose stool; ½ caplet after each subsequent loose stool; but no more than 2 caplets in 24 hours
  children 2-5 years (34 to 47 lbs) | ask a doctor
  children under 2 years (up to 33 lbs) | do not use

Other information

- each caplet contains: calcium 165 mg, sodium 3 mg
- store between 20-25°C (68-77°F). Protect from light.
- do not use if blister unit is torn or broken

Inactive ingredients

acesulfame potassium, croscarmellose sodium, dibasic calcium phosphate, flavor, microcrystalline cellulose, stearic acid

Questions or comments?

call 1-877-895-3665 (toll-free) or 215-273-8755 (collect)

PRINCIPAL DISPLAY PANEL

NDC 50580-338-12

Imodium®
Loperamide HCl, 2 mg /Simethicone, 125 mg Antidiarrheal/Anti-gas

Multi-Symptom Relief
Caplet

Relieves symptoms
of diarrhea plus

- Cramps & Pressure
- Bloating
- Gas

12 Caplets*

*capsule-shaped tablets

Actual Size